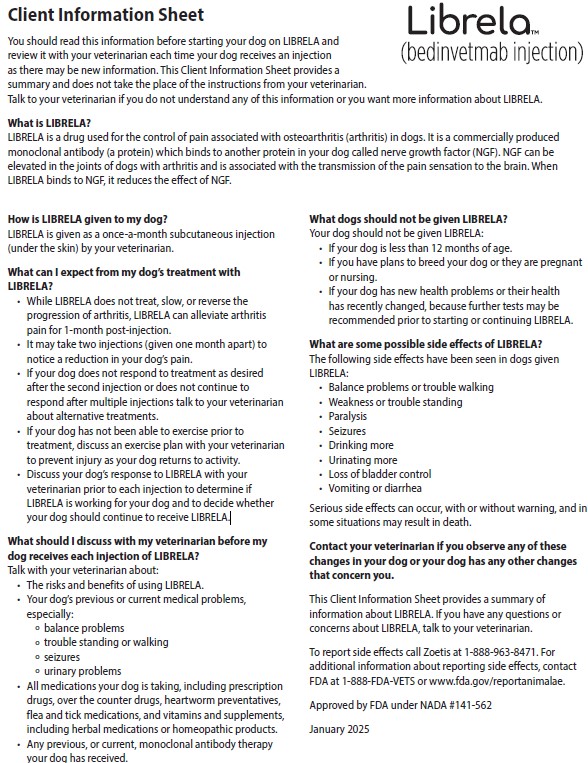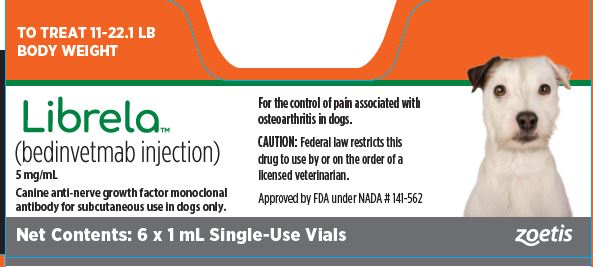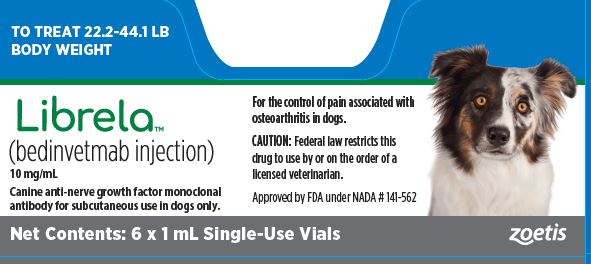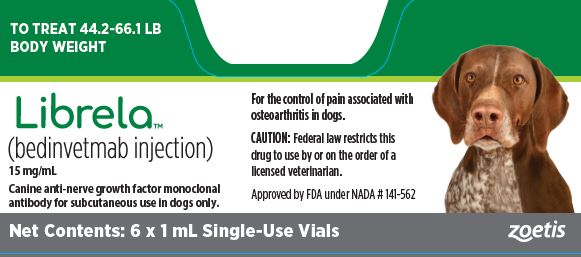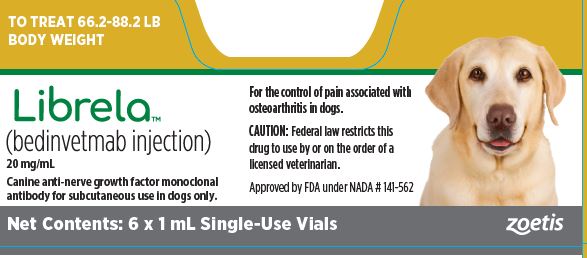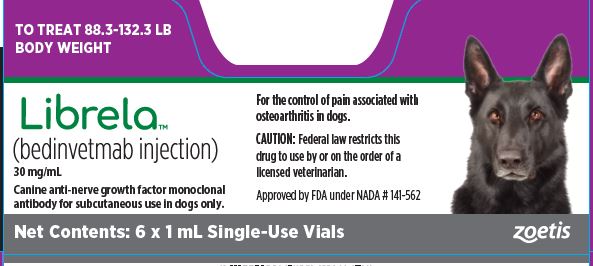 DRUG LABEL: Librela
NDC: 54771-2772 | Form: INJECTION, SOLUTION
Manufacturer: Zoetis Inc.
Category: animal | Type: PRESCRIPTION ANIMAL DRUG LABEL
Date: 20250221

ACTIVE INGREDIENTS: BEDINVETMAB 5 mg/1 1

Librela™

Librela™
(bedinvetmab injection)
Canine anti-nerve growth factor monoclonal antibody for subcutaneous use in dogs only.
Single-Use Vial

CAUTION

Federal law restricts this product to use by or on the order of a licensed veterinarian.

DESCRIPTION

LIBRELA (bedinvetmab injection) is a sterile injectable solution containing 5, 10, 15, 20, or 30 mg/mL of bedinvetmab in 20 mM histidine buffer pH 5.0 [(0.027% w/v L- histidine and 0.382% w/v histidine HCl monohydrate), 8.5% w/v trehalose dihydrate, 0.005% w/v disodium EDTA dihydrate, 0.01% w/v L-methionine, and 0.1% w/v poloxamer 188]. Bedinvetmab is a canine IgG monoclonal antibody (mAb), in which the variable regions from canine B cell sequence were joined with canine IgG constant sequences, and is expressed through recombinant DNA techniques in Chinese hamster ovary (CHO) cells. Bedinvetmab binds to nerve growth factor (NGF) to reduce NGF’s effects. Such mAbs are commonly referred to as anti-NGF mAbs.

INDICATION

LIBRELA is indicated for the control of pain associated with osteoarthritis in dogs.

DOSAGE AND ADMINISTRATION

Always provide the Client Information Sheet and discuss potential adverse drug events with the dog owner prior to administering each injection of LIBRELA (see Post-Approval Experience and Information for Dog Owners).

The minimum target dose of LIBRELA is 0.23 mg/lb (0.5 mg/kg) body weight, administered subcutaneously once a month. Dogs should be dosed by weight range according to the specific dosing information below.
The product does not contain a preservative. The full content of each vial is for single-use only. Once punctured, contents of the vial should be used immediately and any remaining solution should be discarded.
Dogs weighing ≥ 11 lb (≥ 5 kg):
Dogs should be dosed by weight range according to the Dosing Table below (Table 1). Dogs are given the full content of 1 or 2 vials of the appropriate concentration based on body weight. Aseptically withdraw the total dose into a single syringe and administer immediately.

Table1. Dosing Table

 |  | Number and Strength (mg/mL) of LIBRELA Vials to be Administered
Dog Body Weight in Pounds (lb) | Dog Body Weight in Kilograms (kg) | 5 mg/mL orange | 10 mg/mL blue | 15 mg/mL green | 20 mg/mL gold | 30 mg/mL purple
11-22.1 | 5-10 | 1 vial
22.2-44.1 | 10.1-20 |  | 1 vial
44.2-66.1 | 20.1-30 |  |  | 1 vial
66.2-88.2 | 30.1-40 |  |  |  | 1 vial
88.3-132.3 | 40.1-60 |  |  |  |  | 1 vial
132.4-176.4 | 60.1-80 |  |  |  | 2 vials
176.5-220.5 | 80.1-100 |  |  |  | 1 vial | 1 vial
220.6-264.6 | 100.1-120 |  |  |  |  | 2 vials

Dogs < 11 lb:
Aseptically withdraw 0.045 mL/lb (0.1 mL/kg) from a 5 mg/mL vial (orange vial) into a single syringe and administer immediately. Discard the vial after the dose has been withdrawn.
Effectiveness may not be achieved until after the second dose (see EFFECTIVENESS).

CONTRAINDICATIONS

LIBRELA should not be administered to dogs with known hypersensitivity to bedinvetmab.
LIBRELA should not be used in breeding dogs or in pregnant or lactating dogs. Immunoglobulin G class antibodies such as LIBRELA can pass through the placental blood barrier and be excreted in milk. Fetal abnormalities, increased rates of stillbirths and increased postpartum fetal mortality were noted in rodents and primates receiving anti-NGF monoclonal antibodies.

WARNINGS

User Safety Warnings
Not for use in humans. Keep this and all drugs out of reach of children.
For use in dogs only.
Hypersensitivity reactions, including anaphylaxis, could potentially occur in the case of accidental self-injection.
In case of accidental self-injection, seek medical advice immediately and show the package leaflet, vial or carton to the physician.
Pregnant women, women trying to conceive, and breastfeeding women should take extreme care to avoid accidental self-injection.
The importance of Nerve Growth Factor in ensuring normal fetal nervous system development is well-established and laboratory studies conducted on nonhuman primates with human anti-NGF antibodies have shown evidence of reproductive and developmental toxicity.

PRECAUTIONS

Administration of monoclonal antibodies may be associated with hypersensitivity reactions and delayed hypersensitivity reactions. If anaphylaxis or other hypersensitivity reaction occurs, discontinue use and institute appropriate therapy.
The safe use of this product with other monoclonal antibodies has not been evaluated. Use with caution in dogs with known hypersensitivity to other immunoglobulin therapy.
Evaluations were not made to determine if interactions occurred between LIBRELA and veterinary vaccines.
Treatment with LIBRELA may result in the formation of anti-bedinvetmab antibodies and potentially the loss of product effectiveness (see IMMUNOGENICITY).
The safe use of anti-NGF monoclonal antibodies with concurrent nonsteroidal anti-inflammatory drugs (NSAIDs) has not been established in dogs. In human clinical trials, rapidly progressing osteoarthritis (RPOA) has been reported in a small number of patients receiving humanized anti-NGF monoclonal antibody therapy. The incidence of these events increased in human patients receiving NSAID treatment long term in combination with an anti-NGF monoclonal antibody. RPOA has not been characterized or reported in dogs.
The safety and effectiveness of LIBRELA has not been evaluated in dogs less than 12 months of age.
LIBRELA has not been studied in dogs that have a history of cruciate ligament rupture within six months before initial product use as these cases were excluded from the field studies.
Long term effects which may occur more than 9 months after the use of LIBRELA have not been evaluated.
NGF is expressed within the heart and vasculature, and the long-term effects of reduced NGF in dogs with cardiac disease are unknown.
Primates receiving high doses of anti-NGF monoclonal antibodies had anatomical changes in postganglionic cell bodies (reduced size and number of neurons). The change in cell body size returned to normal after anti-NGF monoclonal antibody administration was discontinued. NGF is involved in the normal development of sensory and sympathetic nerve fibers in developing animals. This may be important with use of LIBRELA in young growing dogs.

ADVERSE REACTIONS

The safety of LIBRELA was assessed in a masked, controlled 84-day US field study evaluating the effectiveness of LIBRELA for the control of pain associated with osteoarthritis. Enrollment included 272 dogs, 135 dogs treated with LIBRELA and 137 dogs treated with a negative control (sterile saline). The enrolled dogs were at least 1 year of age (1 to 17 years old), weighed between 1.8 to 62.7 kg and were of various breeds or non-purebred. Dogs were dosed at 28-day intervals and received up to three injections. The most common adverse reactions reported during the study are summarized in Table 2 below.
Table 2. Number (%) of Dogs with Adverse Reactions Reported in the US Field Study

Adverse Reaction* | LIBRELA n (%) (Total N = 135) | Negative Control n (%) (Total N = 137)
Urinary tract infection | 15 (11.1) | 11 (8.0)
Bacterial skin infection | 11 (8.1) | 9 (6.6)
Dermatitis | 10 (7.4) | 8 (5.8)
Dermal mass | 8 (5.9) | 5 (3.6)
Erythema | 6 (4.4) | 5 (3.6)
Dermal cyst(s) | 4 (3.0) | 2 (1.5)
Pain on injection | 4 (3.0) | 2 (1.5)
Inappropriate urination** | 4 (3.0) | 1 (0.7)
Histiocytoma | 3 (2.2) | 0 (0.0)
*An adverse reaction may have occurred more than once in a dog; only the first occurrence was counted.
** Of these, two dogs treated with LIBRELA were among those reported with a urinary tract infection.

The safety of LIBRELA was also evaluated in a masked, controlled 84-day European field study evaluating the effectiveness of LIBRELA for the control of pain associated with osteoarthritis. Enrollment included 281 dogs, 138 dogs were treated with LIBRELA and 143 treated with a negative control (sterile saline). The enrolled dogs were at least 1 year of age (1 to 17.5 years old), weighed between 1.7 to 66 kg and were of various breeds or non-purebred. Dogs were dosed at 28-day intervals and received up to three injections. The most common adverse reactions reported during the study are summarized in Table 3 below.
Table 3. Number (%) of dogs with Adverse Reactions Reported in the European Field Study

Adverse Event Reported* | LIBRELA n (%) (Total N = 138) | Negative Control n (%) (Total N = 143)
Increased Blood Urea Nitrogen 19 (13.8) 7 (4.9) (BUN)** | 19 (13.8) | 7 (4.9)
Lethargy | 5 (3.6) | 0 (0.0)
Emesis | 4 (2.9) | 1 (0.7)
Anorexia | 3 (2.2) | 0 (0.0)
Lameness | 3 (2.2) | 1 (0.7)
Cough | 3 (2.2) | 1 (0.7)
*An adverse reaction may have occurred more than once in a dog; only the first occurrence was counted.
** Two dogs treated with LIBRELA suffered serious adverse events and were euthanized during or after study completion: A 13-year old Bichon Frise had pre-existing increased urine protein-creatinine ratio and heart failure that worsened during study; the dog also had an increase in creatinine during the study and was diagnosed with renal failure and was euthanized 3 days after completing the study. An 8-year-old mixed breed dog had pancreatitis and was euthanized on Day 74. The remainder of the dogs that had elevations in the BUN did not have any obvious adverse events associated with this finding.

One dog in the LIBRELA group was diagnosed with pyelonephritis on Day 15; this dog had pre-existing increased serum BUN and creatinine and a recent history of urinary tract infection that was not confirmed resolved prior to enrollment. Non-steroidal anti-inflammatory drugs (NSAIDs) and acetaminophen were initiated on Day 7 for osteoarthritis-associated joint pain but NSAIDs were discontinued on Day 10 due to anorexia and gastroenteritis; azotemia worsened at Day 13 and the dog received no further LIBRELA treatment.
One dog in the LIBRELA group with a history of atopy, developed mild alopecia and mild erythema on the injection site on Days 5 and 23. Both episodes of alopecia and erythema resolved with treatment.
A total of 89 dogs were enrolled in a 6-month, single arm, open labeled, uncontrolled continuation of the EU field study and received monthly subcutaneous injections of LIBRELA. The study provided additional field safety information.
One dog experienced acute gastroenteritis and recovered following treatment for abdominal pain, fever, vomiting, and anorexia. One large breed dog enrolled for stifle osteoarthritis developed acute forelimb lameness that was diagnosed as elbow dysplasia. Two dogs presented with rear limb paresis of unknown etiology, one of whom responded to ongoing NSAID treatment and one who did not.

Post-Approval Experience (2025)

The following adverse events are based on post-approval adverse drug experience reporting for LIBRELA. Not all adverse events are reported to FDA/CVM. It is not always possible to reliably estimate the adverse event frequency or establish a causal relationship to product exposure using these data.
The following adverse events in dogs are categorized in order of decreasing reporting frequency by body system and in decreasing order of reporting frequency within each body system:
Neurological: ataxia, seizures, paresis, proprioception deficits, paralysis
General: anorexia, lethargy, recumbency
Urinary: polydipsia, polyuria/pollakiuria, urinary incontinence
Gastrointestinal: vomiting, diarrhea
Musculoskeletal: muscle weakness, muscle tremors, lameness
In some cases, death (including euthanasia) has been reported as an outcome of the adverse events listed above.

CONTACT INFORMATION

To report suspected adverse drug events, for technical assistance or to obtain a copy of the Safety Data Sheet (SDS), contact Zoetis Inc. at 1-888‑963-8471.

For additional information about reporting adverse drug experience for animal drugs, contact FDA at 1-888-FDA-VETS or www.fda.gov/reportanimalae.

INFORMATION FOR DOG OWNERS

Always provide and review the Client Information Sheet with the dog owner prior to each injection of LIBRELA. Advise owners of the adverse reactions that may occur following the administration of LIBRELA including balance problems, trouble walking, weakness, trouble standing, seizures, drinking more, urinating more, loss of bladder control, vomiting, and diarrhea. Owners should be advised to contact their veterinarian if any of these signs or other signs of illness are observed. Advise dog owners that serious adverse reactions can occur and result in death or euthanasia (see Adverse Reactions and Post-Approval Experience).
Where a dog has not been able to exercise prior to treatment with LIBRELA, there is an increased risk of injury if the dog becomes more active after being treated with LIBRELA. Discuss an exercise plan with the dog owner to return the dog to activity.

CLINICAL PHARMACOLOGY

Mechanism of Action

Bedinvetmab is a recombinant canine monoclonal antibody that binds to nerve growth factor (NGF), reduces NGF binding to the tropomyosin receptor kinase A (TrkA) and p75 neurotrophin receptor (p75NTR) receptors and decreases TrkA signal transduction in cell types involved in pain. In vitro binding studies suggest that bedinvetmab binds with high affinity to NGF but does not bind to other neurotrophins including human neurotrophin-3 (NT-3), canine and human NT-4, and human brain-derived neurotrophic factor (BDNF).
NGF has been found to be elevated in the osteoarthritic joints of dogs. Following a noxious stimulus, inflammatory cytokines and NGF are released by tissues of the joint.
NGF binds to TrkA/p75NTR receptors found on peripheral nerves, immune cells, endothelial cells, synoviocytes, and chondrocytes to induce peripheral sensitization, neurogenic inflammation, and increased pain perception. Bedinvetmab binds to NGF and prevents NGF/TrkA/p75NTR cellular signaling. In in vitro studies, bedinvetmab potently inhibits NGF-mediated signaling as measured by a reduction in TF-1 cell proliferation and functionally blocks NGF-induced neurite outgrowth in rat PC-12 neuronal cells.
NGF binds to TrkA receptors located on immune cells to elicit the release of additional proinflammatory mediators, including NGF itself. These inflammatory mediators lead to further peripheral sensitization involved in pain perception. Bedinvetmab reduces the expression of these inflammatory mediators in rat PC-12 neuronal cells.

Pharmacokinetics

In a 6-month laboratory study of healthy, adult Beagles administered LIBRELA at monthly doses ranging from 1-10 mg/kg, the area under the curve (AUC) and the maximum concentration (Cmax) increased nearly in proportion to dose and steady-state was achieved after approximately 2 doses. In a laboratory pharmacokinetic study in Beagles at 0.5-1.0 mg/kg, peak serum drug levels were observed at 4-7 days after subcutaneous dosing, the mean bioavailability relative to an intravenous dose was approximately 86%, and the elimination half-life was approximately 12 days.
In a field study at the labeled dose in dogs with osteoarthritis, the half-life was highly variable and averaged approximately 19 days (harmonic mean 15.8 days). Steady-state was achieved after 2 doses.
The metabolic pathway of bedinvetmab has not been characterized. As a canine IgG monoclonal antibody, bedinvetmab is expected to be degraded into small peptides and amino acids via catabolic pathways in a manner similar to endogenous IgG.

IMMUNOGENICITY

Antibodies binding to bedinvetmab (i.e., an anti-drug antibody, ADA), were detected using a multi-tiered ADA testing approach (screening, confirmatory, and titration). Testing the confirmed ADA samples for neutralizing activity of bedinvetmab was not performed. Due to limitations of the assay methods performed to evaluate immunogenicity (confirmatory and titration), clinically relevant conclusions or correlations were not determined from the immunogenicity data reported.
In the US Field Effectiveness Study, 267 of 272 enrolled dogs with osteoarthritis were evaluated for immunogenicity after receiving up to 3 doses of LIBRELA. The presence of pre-existing ADAs was confirmed in 5 out of 267 dogs; 4 dogs in the LIBRELA group and 1 dog in the control group. Three of these LIBRELA-treated dogs continued to have ADAs confirmed after treatment with LIBRELA. Of the remaining dogs evaluated for immunogenicity, the presence of ADAs was confirmed on Day 84 in 1 dog in the LIBRELA-treated group and 1 dog in the control group.
In the EU Field Effectiveness Study, 281 of 287 enrolled dogs with osteoarthritis were evaluated for immunogenicity after receiving up to 3 doses of LIBRELA. The presence of pre-existing ADAs was confirmed in 2 out of 281 dogs; both in the control group. Of the other 141 dogs in the control group, the presence of ADA was confirmed in 1 dog after receiving treatment with placebo (on Study Visit Day 56). Of the 138 LIBRELA-treated dogs, the presence of ADA was confirmed in 2 dogs after treatment with LIBRELA (1 dog on Study Visit Day 84 and 1 dog on Study Visit Study Day 28). Eighty-nine LIBRELA-treated dogs continued on with once monthly treatment for an additional six months, and 82 of these dogs were evaluated for immunogenicity after receiving up to 6 additional doses of LIBRELA. The presence of ADA was confirmed in an additional 2 dogs.
In the 6-Month Safety Study, the presence of ADAs was confirmed in 2 out of 8 negative control dogs and no ADAs were confirmed in any of the 24 dogs administered 7 doses of LIBRELA.
The observed incidence of antibody positivity in an assay is highly dependent on several factors including assay sensitivity and specificity, assay methodology, sample handling, timing of sample collection, concomitant medications, and underlying disease. For these reasons, comparison of the incidence of antibodies to LIBRELA with the incidence of antibodies to other products may not be appropriate.

EFFECTIVENESS

The overall evidence, based on the results of two field studies, supports the conclusion that LIBRELA is effective for the control of pain associated with osteoarthritis in dogs when given as a minimum of two doses administered one month apart.
A US field effectiveness study and a European (EU) field effectiveness study were conducted using a similar study design. Both studies included a group administered LIBRELA and a negative control group that was administered sterile saline. The primary effectiveness endpoint was treatment success (Yes/No) at Day 28 based on owner assessment of pain measured on the Canine Brief Pain Inventory (CBPI).^1-2 CBPI treatment success was a secondary endpoint at Days 7, 14, 42, 56 and 84. Treatment success was defined as a reduction of ≥ 2 in Pain Interference Score (PIS) and ≥ 1 in Pain Severity Score (PSS) vs. Day 0. Dogs receiving rescue treatment (e.g., for lack of efficacy (LOE)) or withdrawn for LOE were counted as treatment failures starting on the day of rescue or withdrawal, respectively.
While the studies had similar success rates on Day 28 in the treatment groups administered LIBRELA (48% and 45.2%), the studies had differences in the success rates in the control groups. The success rate in the control group in the US study was 36.1% and the success rate of the control group in the EU study was 17.0%. Based on these results, there was a larger treatment effect size in the EU study as compared to the US study, such that the US study did not demonstrate a significant difference at Day 28. In the EU study, the primary effectiveness variable was successful and met statistical significance at Day 28 (P = 0.0018).
The CBPI data from both studies demonstrated a greater percentage of dogs achieving treatment success in the LIBRELA-treated vs. control groups at Day 42. This success rate was maintained with a third administration at Day 56 through the end of the study at Day 84. Taken together, the US and EU studies establish the effectiveness for LIBRELA (bedinvetmab injection) for the control of pain associated with osteoarthritis in dogs when given as a minimum of two doses administered one month apart.

US Field Effectiveness Study

An 84-day masked, randomized, controlled field study was conducted at 24 US veterinary clinics. The study enrolled 272 client-owned dogs with clinical signs of osteoarthritis confirmed by radiography and orthopedic examination. Enrolled dogs were randomized at an equal ratio into one of two treatment groups: LIBRELA (0.5 mg/kg, n = 135) or control (sterile saline, n = 137) and were treated on Days 0, 28, and 56. Dog age and body weight ranged from 1.0 to 17.0 years and 1.8 to 62.7 kg, respectively. The percentage of dogs considered treatment successes based on the owner CBPI assessment was greater in the LIBRELA-treated dogs compared to the control group for all assessments. The study failed to demonstrate statistical significance for effectiveness at Day 28; however, the difference in the percentage of treatment successes from Day 42 onward demonstrated a clinical effect in the LIBRELA group compared to the control group.
Table 4. Study #1: Least Squares Mean Percent Success by Assessment Day

Day | Group | N | % Success
7 | LIBRELA | 125 | 30.3
 | Control | 129 | 24.8
14 | LIBRELA | 129 | 41.4
 | Control | 130 | 30.5
28 | LIBRELA | 128 | 48.0
 | Control | 131 | 36.1
42 | LIBRELA | 121 | 54.8
 | Control | 126 | 38.9
56 | LIBRELA | 122 | 57.8
 | Control | 124 | 42.1
84 | LIBRELA | 118 | 57.1
 | Control | 118 | 33.4

EU Field Effectiveness Study

An 84-day masked, randomized, controlled field study was conducted at 26 different study sites located in Portugal, Hungary, Ireland and Germany. The study enrolled 287 client-owned dogs with clinical signs of osteoarthritis confirmed by radiography and orthopedic examination. Dogs were randomized at an equal ratio into one of two treatment groups: LIBRELA (0.5 mg/kg, n = 141) or control (sterile saline, n = 146) and were treated on Days 0, 28, and 56. Dog age and body weight ranged from 1.0 to 17.5 years and 1.7 to 66.0 kg, respectively. The percentage of dogs considered treatment successes based on the owner CBPI assessment was greater for LIBRELA-treated dogs compared to the control group for all assessments. The study met statistical significance compared to the control at Day 28 (primary effectiveness endpoint; P = 0.0018). The difference in the percentage of treatment successes from Day 42 onward continued to demonstrate a clinical effect in the LIBRELA group compared to the control group.
Table 5. Study #2: Least Squares Mean Percent Success by Assessment Day

Day | Group | N | % Success
7 | LIBRELA | 128 | 18.5
 | Control | 130 | 4.0
14 | LIBRELA | 132 | 35.7
 | Control | 132 | 9.6
28 | LIBRELA | 131 | 45.2
 | Control | 131 | 17.0
42 | LIBRELA | 133 | 53.5
 | Control | 134 | 21.4
56 | LIBRELA | 133 | 52.9
 | Control | 134 | 20.6
84 | LIBRELA | 129 | 49.9
 | Control | 132 | 24.3

TARGET ANIMAL SAFETY

6 Month Margin of Safety Study:

LIBRELA (bedinvetmab injection) 15 mg/mL and 30 mg/mL concentrations were administered subcutaneously to 11 to 12-month old, healthy Beagles (8 dogs per group) at doses of 1 mg/kg (1X), 3 mg/kg (3X), and 10 mg/kg (10X) every 28 days for seven consecutive doses. The control group (8 dogs) received sterile saline injections. Dogs weighed 5.6-11.7 kg at study initiation.

There were no clinically significant changes noted in neurological examinations, body temperature, heart and respiratory rate, blood pressure, electrocardiography, and organ weights. Detailed pathology evaluation of the shoulder, elbow, hip, and knee joints were conducted.

Vomiting and soft stool were noted across all groups throughout the study. Scabbing on the face, neck and thorax was seen across all groups except the 1 mg/kg group. Injection site redness was noted sporadically for 1 control dog, 2 dogs in the 1 mg/kg treatment group, 5 dogs in the 3 mg/kg treatment group, and 5 dogs in the 10 mg/kg treatment group. One dog in the 3 mg/kg treatment group had a temporary, mild swollen facial area 26 days after the first dose that resolved spontaneously. Two dogs in the 3 mg/kg treatment group had lymphadenopathy on the last study day with no related histopathology findings. One dog in the 10 mg/kg treatment group had an approximately 2.5 cm X 3.5 cm circular raised firm erythematous lesion with slight serosanguinous discharge and mild scabs of the shaved cervical area that resolved over 14 days.

One dog in the 1 mg/kg treatment group had an increasing ALP value over the course of the study that increased threefold above the high end of the reference range at study completion. There was no gross or histopathology correlate.

One dog in the 1 mg/kg treatment group had mild cartilage necrosis in the left ulna and an erosion in the cartilage of the right ulna. One dog in the 3 mg/kg treatment group had mild bilateral, femoral neck enthesophytes observed on radiographs pre-treatment. On end of study radiography and pathology evaluation, this dog had an osteophyte of the left acetabulum, mild left acetabulum remodeling and severe left femoral neck enthesophytes. Microscopically, mild to moderate cartilage degeneration with erosion and proteoglycan depletion was also noted in the left proximal femur and acetabulum. The mild right femoral neck enthesophytes were the same grade as pre-treatment. The findings may be progression of an underlying musculoskeletal condition; however, a potential relation to treatment cannot be ruled out.

None of the LIBRELA-treated dogs developed anti-drug antibodies due to bedinvetmab administration.

Additional Safety Studies:

In a two-week laboratory safety study, eight dogs concurrently received one subcutaneous injection of LIBRELA at the high end of the inherent dose band (1 mg/kg) and fourteen days of an injectable NSAID. This limited laboratory study did not provide sufficient data to support a conclusion on the safety of concurrent use of LIBRELA and NSAIDs.

In a 3-month exploratory laboratory safety study using a non-final formulation of bedinvetmab administered by subcutaneous injection monthly for four doses, a dog administered a 4 mg/kg dose had a reddened and/or swollen muzzle abrasion, with an elevated white blood cell count, and elevated globulin level and fibrinogen level. At one of the injection administrations, one dog administered a 4 mg/kg dose had a 4 cm X 2 cm injection site erythema with an eschar that resolved; and one dog administered a 1 mg/kg dose had 3 cm X 1 cm injection site erythema that resolved. Another dog administered a 1 mg/kg dose had injection site erythema, scabbing, and mucopurulent discharge for 18 days.

STORAGE CONDITIONS

LIBRELA (bedinvetmab injection) should be stored in a refrigerator, 2° – 8°C (36° – 46° F). Do not freeze. Store vials in their boxes to protect from prolonged exposure to light. Once punctured, contents of the vial should be used immediately and any remaining solution should be discarded.

HOW SUPPLIED

LIBRELA is available in 5 strengths packaged in 4 mL glass vials containing an extractable volume of 1 mL of clear solution. Each strength is available in cartons containing 2 or 6 vials.

REFERENCES

1. Brown DC, Bell M, Rhodes L. Power of treatment success definitions when the Canine Brief Pain Inventory is used to evaluate carprofen treatment for the control of pain and inflammation in dogs with osteoarthritis. Amer J Vet Rsch 2013; 74(12):1467-1473.
2. Brown DC, Bell M, Rhodes L. ERRATUM to: Power of treatment success definitions when the Canine Brief Pain Inventory is used to evaluate carprofen treatment for the control of pain and inflammation in dogs with osteoarthritis. Amer J Vet Rsch 2014; 75(4):353.

Approved by FDA under NADA # 141-562
Distributed by:
Zoetis Inc.
Kalamazoo, MI 49007
January 2025
30007554

Client Information Sheet

30007554

PRINCIPAL DISPLAY PANEL - 5mg carton

40041800

PRINCIPAL DISPLAY PANEL - 10mg carton

40041801

PRINCIPAL DISPLAY PANEL - 15mg carton

40041802

PRINCIPAL DISPLAY PANEL - 20mg carton

40041803

PRINCIPAL DISPLAY PANEL - 30mg carton

40041804